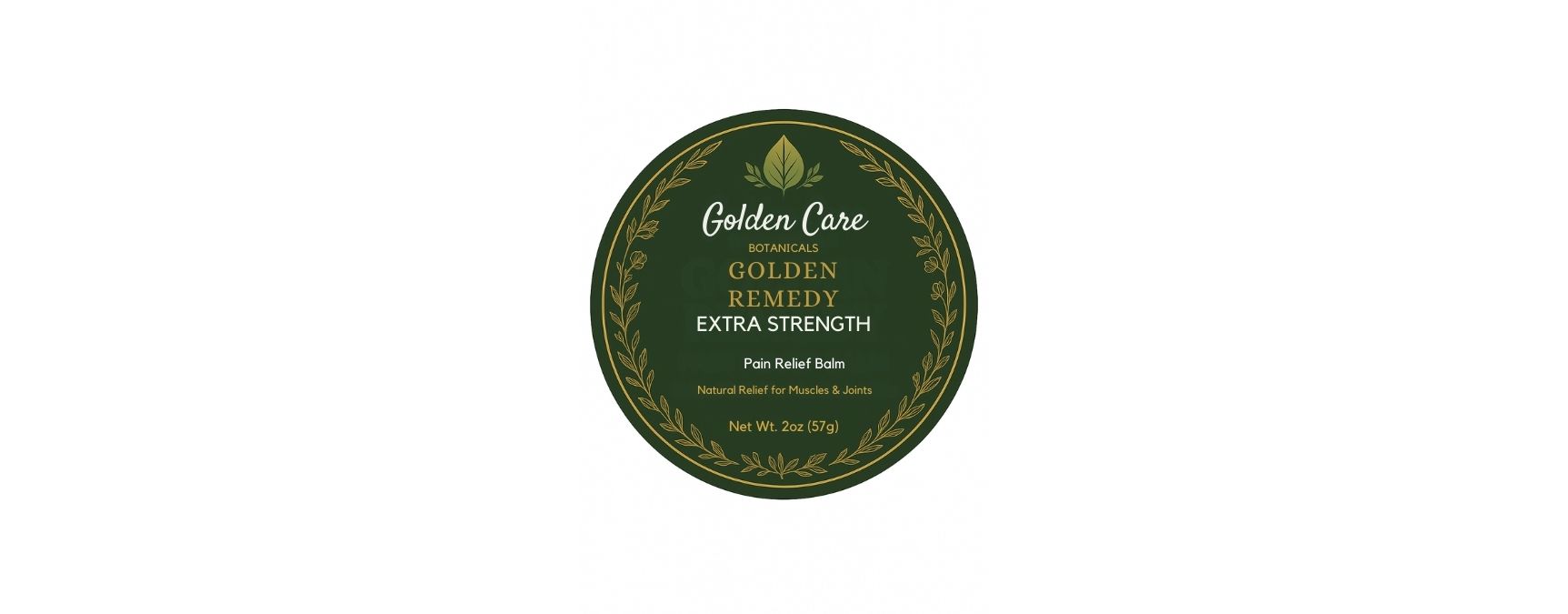 DRUG LABEL: Golden Remedy Extra Strength
NDC: 87037-002 | Form: SALVE
Manufacturer: Golden Care Botanicals LLC
Category: otc | Type: HUMAN OTC DRUG LABEL
Date: 20250926

ACTIVE INGREDIENTS: MENTHOL 6.5 g/6.5 g; CAMPHOR (NATURAL) 6.5 g/6.5 g
INACTIVE INGREDIENTS: COCOA BUTTER; BUTYROSPERMUM PARKII (SHEA) BUTTER; MANGIFERA INDICA SEED BUTTER; HELICHRYSUM GYMNOCEPHALUM WHOLE; CINNAMON LEAF OIL; GINGER OIL; AVOCADO OIL; BLACK PEPPER OIL; CLOVE OIL; BEESWAX; FRANKINCENSE; .ALPHA.-TOCOPHEROL ACETATE, D-; PERSEA GRATISSIMA (AVOCADO) SEED

ACTIVE INGREDIENT

Menthol 4.3%................External analgesic

Camphor 4.3%..............External analgesic

PURPOSE

Topical analgesic for temporary relief of pain/itching due to sunburn, minor burns, insect bites, and everyday aches

DO NOT USE

Don not use on open wounds, broken skin, or with a heating pad

WARNINGS

For external use only

Stop use and ask a medical doctor if condition worsens, or symptoms persist

INACTIVE INGREDIENT

Inactive ingredients: Aaloe vera juice, Witch hazel, Avocado oil, Menthol crystals, Camphor, Ginger essential oil, Frankincense essential oil, Helichrysum essential oil, Optiphen, and Vitamin E

DOSAGE AND ADMINISTRATION

Directions: Adults and children 12+ years and older. Apply to affected area not more than 3-4 times per day

INDICATIONS AND USAGE

Route of administration: Topical

KEEP OUT OF REACH OF CHILDREN

If swallowed, seek immediate medical attention or contact Poison Control